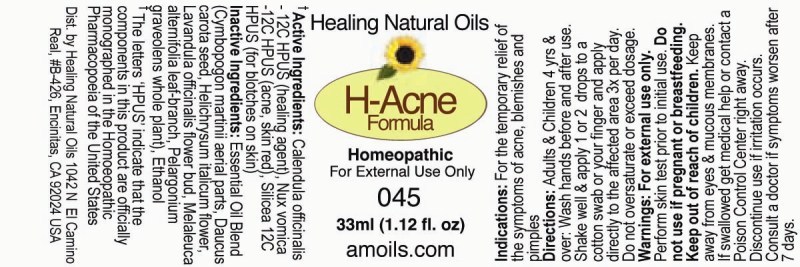 DRUG LABEL: H Acne Formula
NDC: 57520-1111 | Form: OIL
Manufacturer: Apotheca Company
Category: homeopathic | Type: HUMAN OTC DRUG LABEL
Date: 20120313

ACTIVE INGREDIENTS: CALENDULA OFFICINALIS FLOWERING TOP 12 [hp_C]/1 mL; STRYCHNOS NUX-VOMICA SEED 12 [hp_C]/1 mL; SILICON DIOXIDE 12 [hp_C]/1 mL
INACTIVE INGREDIENTS: TEA TREE OIL; PALMAROSA OIL; LAVENDER OIL; GERANIUM OIL, ALGERIAN TYPE; CARROT SEED OIL; HELICHRYSUM ITALICUM FLOWER OIL; ALCOHOL

H-Acne Formula

ACTIVE INGREDIENT

ACTIVE INGREDIENTS: alendula officinalis 12C HPUS, Nux vomica 12C HPUS, Silicea 12C HPUS.

PURPOSE

INDICATIONS: For the temporary relief of the symptoms of acne, blemishes and pimples.

WARNINGS: For external use only.

Perform skin test prior to initial use.

Do not use if pregnant or breastfeeding.

Keep out of reach of children. Keep away from eyes and mucous membranes. If swallowed get medical help or contact a Poison Control Center right away.

Discontinue use if irritations occurs.

Consult a doctor if symptoms worsen after 7 days.

DOSAGE AND ADMINISTRATION

DIRECTIONS: Adults and Children 4 yrs and over: Wash hands before and after use. Shake well and apply 1 or 2 drops to a cotton swab or your finger and apply directly to the affected area 3x per day. Do not oversaturate or exceed dosage.

INACTIVE INGREDIENT

INACTIVE INGREDIENTS: Cymbopogon martinii aerial parts, Daucus carota seed, Helichrysum italicum flower, Lavandula officinalis flower bud, Melaleuca alternifolia leaf-branch, Pelargonium graveolens whole plant, Ethanol.

KEEP OUT OF REACH OF CHILDREN. Keep away from eyes and mucous membranes. If swallowed get medical help or contact a Poison Control Center right away.

INDICATIONS AND USAGE

INDICATIONS: For the temporary relief of the symptoms of acne, blemishes and pimples.

QUESTIONS

Dist. by Healing Natural Oils

1042 N El Camino Real #B-426

Encinitas, CA 92024 USA

The letters "HPUS" indicate that the components in this product are officially monographed in the Homeopathic Pharmacopoeia of the United States.

PACKAGE LABEL

Healing Natural Oils

H Acne Formula

Homeopathic

For External Use Only

045

33ml (1.12 fl. oz)